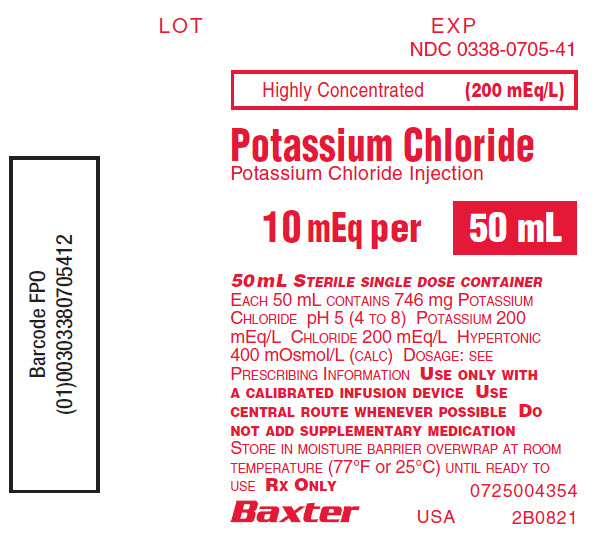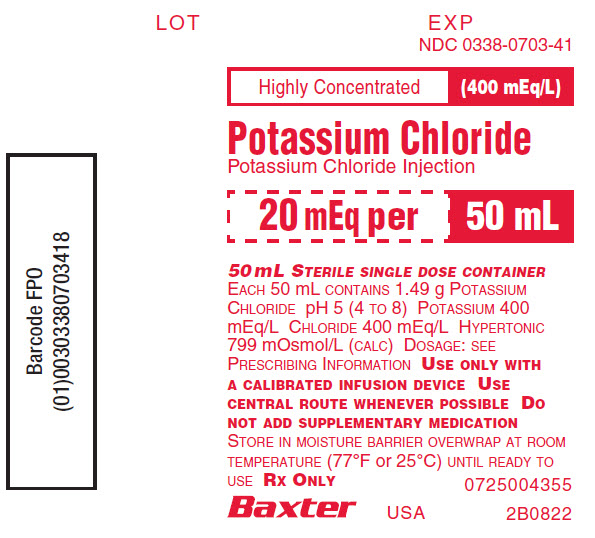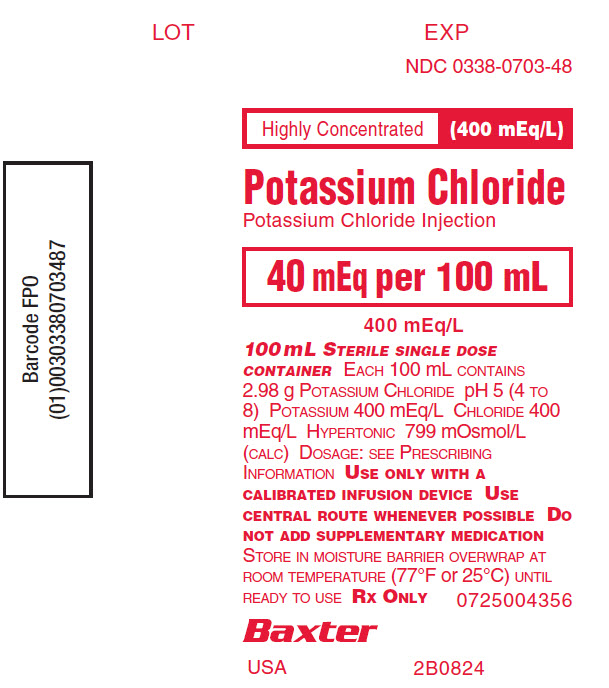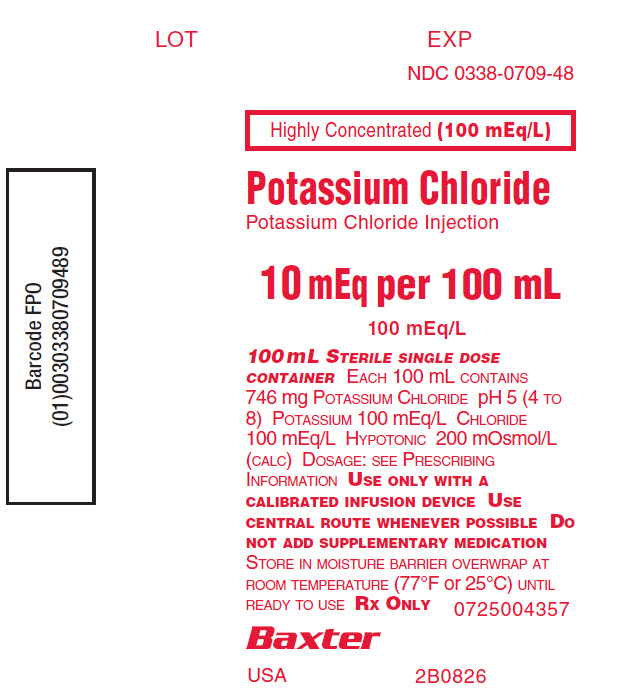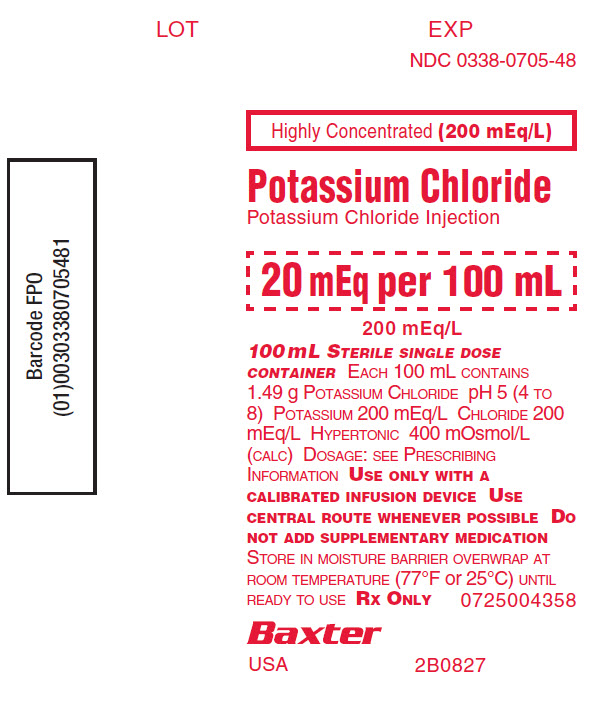 DRUG LABEL: Potassium Chloride
NDC: 0338-0703 | Form: INJECTION, SOLUTION
Manufacturer: Baxter Healthcare Corporation
Category: prescription | Type: HUMAN PRESCRIPTION DRUG LABEL
Date: 20240613

ACTIVE INGREDIENTS: POTASSIUM CHLORIDE 29.8 g/1000 mL
INACTIVE INGREDIENTS: WATER

For Use Only with a Calibrated Infusion Device
Highly Concentrated
Potassium Chloride Injection
in Plastic Container
Ready To Use
VIAFLEX Plus Container

DESCRIPTION

This Potassium Chloride Injection, is a sterile, nonpyrogenic, highly concentrated, ready-to-use, solution of Potassium Chloride, USP in Water for Injection, USP for electrolyte replenishment in a single dose container for intravenous administration. It contains no antimicrobial agents.

Potassium Chloride Injection mEq Potassium/Container | Composition (g/L) Potassium Chloride, USP (KCl) | Osmolarity [Normal physiologic osmolarity range is approximately 280 to 310 mOsmol/L. Administration of substantially hypertonic solutions (≥ 600 mOsmol/L) may cause vein damage.] (mOsmol/L) (calc) | pH | Ionic Concentration (mEq/L)
Potassium Chloride Injection mEq Potassium/Container | Composition (g/L) Potassium Chloride, USP (KCl) | Osmolarity [Normal physiologic osmolarity range is approximately 280 to 310 mOsmol/L. Administration of substantially hypertonic solutions (≥ 600 mOsmol/L) may cause vein damage.] (mOsmol/L) (calc) | pH | Potassium | Chloride
10 mEq/100 mL | 7.46 | 200 | 5.0 (4.0 to 8.0) | 100 | 100
10 mEq/50 mL 20 mEq/100 mL | 14.9 | 400 | 5.0 (4.0 to 8.0) | 200 | 200
20 mEq/50 mL 40 mEq/100 mL | 29.8 | 799 | 5.0 (4.0 to 8.0) | 400 | 400

This VIAFLEX Plus plastic container is fabricated from a specially formulated polyvinyl chloride (PL 146 Plastic). Exposure to temperatures above 25°C/77°F during transport and storage will lead to minor losses in moisture content. Higher temperatures lead to greater losses. It is unlikely that these minor losses will lead to clinically significant changes within the expiration period. The amount of water that can permeate from inside the container into the overwrap is insufficient to affect the solution significantly. Solutions in contact with the plastic container may leach out certain of its chemical components from the plastic in very small amounts; however, biological testing was supportive of the safety of the plastic container materials.

CLINICAL PHARMACOLOGY

Potassium is the major cation of body cells (160 mEq/liter of intracellular water) and is concerned with the maintenance of body fluid composition and electrolyte balance. Potassium participates in carbohydrate utilization, protein synthesis, and is critical in the regulation of nerve conduction and muscle contraction, particularly in the heart. Chloride, the major extracellular anion, closely follows the metabolism of sodium, and changes in the acid-base of the body are reflected by changes in the chloride concentration.

Normally about 80 to 90% of the potassium intake is excreted in the urine, the remainder in the stools and to a small extent, in the perspiration. The kidney does not conserve potassium well so that during fasting, or in patients on a potassium-free diet, potassium loss from the body continues resulting in potassium depletion. A deficiency of either potassium or chloride will lead to a deficit of the other.

INDICATIONS AND USAGE

Potassium Chloride Injection is indicated in the treatment of potassium deficiency states when oral replacement is not feasible.

THIS HIGHLY CONCENTRATED, READY-TO-USE POTASSIUM CHLORIDE INJECTION IS INTENDED FOR THE MAINTENANCE OF SERUM K^+ LEVELS AND FOR POTASSIUM SUPPLEMENTATION IN FLUID RESTRICTED PATIENTS WHO CANNOT ACCOMMODATE ADDITIONAL VOLUMES OF FLUID ASSOCIATED WITH POTASSIUM SOLUTIONS OF LOWER CONCENTRATION.

When using these products, these patients should be on continuous cardiac monitoring and frequent testing for serum potassium concentration and acid-base balance.

CONTRAINDICATIONS

Potassium Chloride Injection is contraindicated in patients with:

- hyperkalemia
- known hypersensitivity to Potassium Chloride Injection

WARNINGS

Hyperkalemia

THIS HIGHLY CONCENTRATED, READY-TO-USE POTASSIUM CHLORIDE INJECTION IS INTENDED FOR THE MAINTENANCE OF SERUM K^+ LEVELS AND FOR POTASSIUM SUPPLEMENTATION IN FLUID RESTRICTED PATIENTS WHO CANNOT ACCOMMODATE ADDITIONAL VOLUMES OF FLUID ASSOCIATED WITH POTASSIUM SOLUTIONS OF LOWER CONCENTRATION.

TO AVOID POTASSIUM INTOXICATION, DO NOT INFUSE THESE SOLUTIONS RAPIDLY.

Potassium Chloride Injection should be administered with extreme caution, if at all, to patients with conditions predisposing to hyperkalemia and/or associated with increased sensitivity to potassium, such as patients with:

- severe renal impairment,
- acute dehydration,
- extensive tissue injury or burns,
- certain cardiac disorders such as congestive heart failure or AV block,
- potassium-aggravated skeletal muscle channelopathies (e.g., hyperkalemic periodic paralysis, paramyotonia congenita, and potassium-aggravated myotonia/paramyotonia).

Potassium Chloride Injection should be administered with caution to patients who are at risk of experiencing hyperosmolality, acidosis, or undergo correction of alkalosis (conditions associated with a shift of potassium from intracellular to extracellular space) and patients treated concurrently or recently with agents or products that can cause hyperkalemia (see PRECAUTIONS, Drug Interactions).

If used in high-risk patients, especially close monitoring and careful dose selection and adjustment is required.

PATIENTS REQUIRING HIGHLY CONCENTRATED SOLUTIONS SHOULD BE KEPT ON CONTINUOUS CARDIAC MONITORING AND UNDERGO FREQUENT TESTING FOR SERUM POTASSIUM AND ACID-BASE BALANCE, ESPECIALLY IF THEY RECEIVE DIGITALIS.

Administration of concentrated potassium solutions can cause cardiac conduction disorders (including complete heart block) and other cardiac arrhythmias at any time during infusion. Continuous cardiac monitoring is performed to aid in the detection of cardiac arrhythmias due to a sudden increase in serum potassium concentration (e.g., when potassium infusion is started), or transient or sustained hyperkalemia (see ADVERSE REACTIONS and OVERDOSAGE).

Frequently, mild or moderate hyperkalemia is asymptomatic and may be manifested only by increased serum potassium concentrations and, possibly, characteristic EKG changes. However, fatal arrhythmias can develop at any time during hyperkalemia.

Serum potassium levels are not necessarily indicative of tissue potassium levels.

Tissue Damage and Thrombophlebitis

When infusing concentrated potassium solutions, including Potassium Chloride Injection, care must be taken to prevent paravenous administration or extravasation because such solutions may be associated with tissue damage, which may be severe and include vascular, nerve, and tendon damage, leading to surgical intervention, including amputation. Secondary complications including pulmonary embolism from thrombophlebitis have been reported as a consequence of tissue damage from potassium chloride.

Administer intravenously only with a calibrated infusion device at a slow, controlled rate. (see DOSAGE AND ADMINISTRATION). Highest concentrations (400 mEq per L) should be exclusively administered via central intravenous route. Whenever possible, administration via a central route is recommended for all concentrations of Potassium Chloride Injection for thorough dilution by the blood stream and decreasing the risk of extravasation and to avoid pain and phlebitis associated with peripheral infusion. Correct placement of the catheter should be verified before administration.

Hyponatremia

Monitoring of serum sodium is particularly important for hypotonic fluids. Potassium Chloride Injection has an osmolarity of 200 to 799 mOsmol/L (see DESCRIPTION).

Potassium Chloride Injection may cause hyponatremia. The risk for hyponatremia is increased, in pediatric patients, elderly patients, postoperative patients, those with psychogenic polydipsia and in patients treated with medications that increase the risk of hyponatremia (such as certain diuretic, antiepileptic and psychotropic medications) (see PRECAUTIONS, Drug Interactions).

Acute hyponatremia can lead to acute hyponatremic encephalopathy characterized by headache, nausea, seizures, lethargy and vomiting. Patients with brain edema are at particular risk of severe, irreversible and life-threatening brain injury.

Avoid Potassium Chloride Injection in patients with or at risk for hyponatremia. If use cannot be avoided, monitor serum sodium concentrations.

High volume infusion must be used with close monitoring in patients with cardiac or pulmonary failure, and in patients with non-osmotic vasopression release (including SIADH), due to the risk of hospital-acquired hyponatremia.

Fluid Overload

Depending on the volume and rate of infusion, and the patient’s underlying clinical condition, the intravenous administration of Potassium Chloride Injection can cause electrolyte disturbances such as overhydration/hypervolemia and congested states including central (e.g., pulmonary edema) and peripheral edema.

Avoid Potassium Chloride Injection in patients with or at risk for fluid and/or solute overloading. If use cannot be avoided, monitor fluid balance, electrolyte concentrations and acid base balance as needed and especially during prolonged use.

Hyperchloremia

In patients with or at risk of hyperchloremia, Potassium Chloride Injection may exacerbate or result in hyperchloremia. Monitor plasma chloride levels and renal function in such patients.

PRECAUTIONS

General

Do not connect flexible plastic containers in series in order to avoid air embolism due to possible residual air contained in the primary container.

Laboratory Tests

Serum potassium levels are not necessarily indicative of tissue potassium levels.

Clinical evaluation and periodic laboratory determinations are necessary to monitor changes in fluid balance, electrolyte concentrations, and acid-base balance during prolonged parenteral therapy or whenever the condition of the patient warrants such evaluation. Significant deviations from normal concentrations may require the use of additional electrolyte supplements, or the use of electrolyte-free dextrose solutions to which individualized electrolyte supplements may be added.

Drug Interactions

Other Products that Cause Hyperkalemia

Administration of Potassium Chloride Injection in patients treated concurrently or recently with other products that can cause hyperkalemia or increase the risk of hyperkalemia (e.g., potassium-sparing diuretics, ACE inhibitors, angiotensin II receptor antagonists, cyclosporine and tacrolimus) increases the risk of severe and potentially fatal hyperkalemia, in particular in the presence of other risk factors for hyperkalemia (see WARNINGS). Avoid use of Potassium Chloride injection in patients receiving such products. If use cannot be avoided, monitor serum potassium concentrations.

Other Drugs that Increase the Risk of Hyponatremia

Administration of Potassium Chloride Injection in patients treated concomitantly with drugs associated with hyponatremia may increase the risk of developing hyponatremia (see WARNINGS). Avoid use of Potassium Chloride Injection in patients receiving drugs that may increase the risk of hyponatremia, such as diuretics and antiepileptics. Drugs that increase the vasopressin effect reduce renal electrolyte free water excretion and may also increase the risk of hyponatremia following treatment with intravenous fluids.

If use cannot be avoided, monitor serum sodium concentrations.

Pregnancy

There are no adequate, well controlled studies with Potassium Chloride Injection in pregnant women and animal reproduction studies have not been conducted with this drug. Therefore, it is not known whether potassium chloride injection can cause fetal harm when administered to a pregnant woman. Potassium Chloride Injection should be given during pregnancy only if potential benefit justifies the potential risk to the fetus.

Nursing Mothers

It is not known whether this drug is present in human milk. Because many drugs are present in human milk, caution should be exercised when Potassium Chloride Injection is administered to a nursing mother.

Pediatric Use

These products should not be used in children at this time. Safety and effectiveness of Potassium Chloride Injection in pediatric patients have not been established by adequate and well-controlled studies.

ADVERSE REACTIONS

The following adverse reactions associated with the use of Potassium Chloride Injection were identified in postmarketing reports. Because these reactions were reported voluntarily from a population of uncertain size, it is not always possible to estimate their frequency, reliably, or to establish a causal relationship to drug exposure.

Immune system disorders: Hypersensitivity, as manifested by rash and angioedema

Metabolism and nutrition disorders: Hyperkalemia, hyponatremia

Cardiac disorders: Cardiac arrest*, asystole*, ventricular fibrillation*, bradycardia

*as a manifestation of rapid intravenous administration and/or of hyperkalemia

Respiratory, Thoracic, and Mediastinal Disorders: Dyspnea

General disorders and administration site conditions: Chest pain, infusion site thrombosis, infusion site phlebitis, infusion site erythema, infusion site swelling, infusion site pain, infusion site irritation, and/or a burning sensation.

Nervous System Disorders: Hyponatremic encephalopathy

The following adverse reactions were reported in association with extravasation: Skin necrosis, skin ulcer, soft tissue necrosis, muscle necrosis, nerve injury, tendon injury, and vascular injury.

OVERDOSAGE

Potassium overdose can cause potentially fatal hyperkalemia. Manifestations of hyperkalemia include:

- Disturbances in cardiac conduction and arrhythmias, including bradycardia, heart block, asystole, ventricular tachycardia, ventricular fibrillation
- Hypotension
- Muscle weakness up to and including muscular and respiratory paralysis, paresthesia
- Gastrointestinal symptoms (ileus, nausea, vomiting, abdominal pain)

Frequently, mild or moderate hyperkalemia is asymptomatic and may be manifested only by increased serum potassium concentrations and, possibly, characteristic electrocardiographic changes. However, fatal arrhythmias can develop at any time.

In addition to arrhythmias and conduction disorders, the EKG shows progressive changes that occur with increasing potassium levels. Possible changes include:

- peaking of T waves,
- loss of P waves, and
- QRS widening.

However, the correlation between potassium levels and EKG changes is not precise, and whether or at which potassium level certain EKG signs develop depends on factors such as patient sensitivity, the presence of other electrolyte disorders, and the rapidity of the development of hyperkalemia.

The presence of any EKG findings that are suspected to be caused by hyperkalemia should be considered a medical emergency.

In the event of hyperkalemia, discontinue the infusion immediately and institute close EKG, laboratory and other monitoring and, as necessary, corrective therapy to reduce serum potassium levels as necessary. The use of potassium containing foods or medications must also be eliminated.

Treatment of mild to severe hyperkalemia with signs and symptoms of potassium intoxication includes the following:

1. Dextrose Injection, USP, 10% or 25%, containing 10 units of crystalline insulin per 20 grams of dextrose administered intravenously, 300 to 500 mL per hour.
2. Absorption and exchange of potassium using sodium or ammonium cycle cation exchange resin, orally and as retention enema.
3. Hemodialysis and peritoneal dialysis.

In cases of digitalization, too rapid a lowering of plasma potassium concentration can cause digitalis toxicity.

DOSAGE AND ADMINISTRATION

The dose and rate of administration are dependent upon the specific condition of each patient.

Administer intravenously only with a calibrated infusion device at a slow, controlled rate. Highest concentrations (400 mEq/L) should be exclusively administered via central intravenous route. Whenever possible, administration via a central route is recommended for all concentrations of Potassium Chloride Injection for thorough dilution by the blood stream and decreasing the risk of extravasation and to avoid pain and phlebitis associated with peripheral infusion (see WARNINGS). Correct placement of the catheter should be verified before administration.

Recommended administration rates should not usually exceed 10 mEq per hour or 200 mEq for a 24 hour period if the serum potassium level is greater than 2.5 mEq per liter.

In urgent cases where the serum potassium level is less than 2.0 mEq per liter or where severe hypokalemia is a threat, (serum potassium level less than 2.0 mEq per liter and electrocardiographic changes and/or muscle paralysis) rates up to 40 mEq per hour or 400 mEq over a 24 hour period can be administered very carefully when guided by continuous monitoring of the EKG and frequent serum K^+ determinations to avoid hyperkalemia and cardiac arrest.

Parenteral drug products should be inspected visually for particulate matter and discoloration, whenever solution and container permit. Do not administer unless solution is clear and seal is intact. Use of a final filter is recommended during administration of all parenteral solutions where possible.

Do not add supplementary medication.

HOW SUPPLIED

Potassium Chloride Injection in VIAFLEX Plus plastic containers is available as follows:

2B0826 | 10 mEq/100 mL | NDC 0338-0709-48
2B0821 | 10 mEq/50 mL | NDC 0338-0705-41
2B0827 | 20 mEq/100 mL | NDC 0338-0705-48
2B0822 | 20 mEq/50 mL | NDC 0338-0703-41
2B0824 | 40 mEq/100 mL | NDC 0338-0703-48

Exposure of pharmaceutical products to heat should be minimized. Avoid excessive heat. It is recommended that this product be stored at room temperature (25°C).

DIRECTIONS FOR USE OF VIAFLEX PLUS PLASTIC CONTAINER

See PRECAUTIONS for information on the avoidance of air embolism.

To Open

Tear overwrap down side at slit and remove solution container. Visually inspect the container. If the outlet port protector is damaged, detached, or not present, discard container as solution path sterility may be impaired. Some opacity of the plastic due to moisture absorption during the sterilization process may be observed. This is normal and does not affect the solution quality or safety. The opacity will diminish gradually. Check for minute leaks by squeezing inner bag firmly. If leaks are found, discard solution as sterility may be impaired.

Preparation for Administration

1. Suspend container from eyelet support.
2. Remove plastic protector from outlet port at bottom of container.
3. Attach administration set. Refer to complete directions accompanying set.

Baxter Healthcare Corporation
Deerfield, IL 60015 USA
Printed in USA

Baxter, PL 146 and Viaflex are trademarks of Baxter International Inc.

07-19-00-3141
Rev. 06/2022

PRINCIPAL DISPLAY PANEL

Container Label

Container Label

LOT EXP

NDC 0338-0705-41

Highly Concentrated (200 mEq/L)
Potassium Chloride
Potassium Chloride Injection
10 mEq per 50 mL
50 mL STERILE SINGLE DOSE CONTAINER
EACH 50 mL CONTAINS 746 mg g POTASSIUM
CHLORIDE pH 5 (4 TO 8) POTASSIUM 200
mEq/L CHLORIDE 200 mEq/L HYPERTONIC
400 mOsmol/L (CALC) DOSAGE: SEE
PRESCRIBING INFORMATIONUSE ONLY
WITH A CALIBRATED INFUSION DEVICE USE
CENTRAL ROUTEWHENEVER POSSIBLE DO
NOT ADD SUPPLEMENTARY MEDICATION
STORE IN MOISTURE BARRIER OVERWRAP AT ROOM
TEMPERATURE (77°F or 25°C) UNTIL READY TO
USE Rx ONLY 0725004354

BAXTER Logo USA 2B0821

Barcode FPO
(01)00303380705412

Container Label

Container Label

LOT EXP

NDC 0338-0703-41

Highly Concentrated (400 mEq/L)
Potassium Chloride
Potassium Chloride Injection
20 mEq per 50 mL
50 mL STERILE SINGLE DOSE CONTAINER
EACH 50 mL CONTAINS 1.49 g POTASSIUM
CHLORIDE pH 5 (4 TO 8) POTASSIUM 400
mEq/L CHLORIDE 400 mEq/L HYPERTONIC
799 mOsmol/L (CALC) DOSAGE: SEE
PRESCRIBING INFORMATIONUSE ONLY WITH
A CALIBRATED INFUSION DEVICE USE
CENTRAL ROUTE WHENEVER POSSIBLE DO
NOT ADD SUPPLEMENTARY MEDICATION
STORE IN MOISTURE BARRIER OVERWRAP AT ROOM
TEMPERATURE (77°F or 25°C) UNTIL READY TO
USE Rx ONLY 0725004355

BAXTER Logo USA 2B0822

Barcode FPO
(01)00303380703418

Container Label

Container Label

LOT EXP

NDC 0338-0703-48

Highly Concentrated (400 mEq/L)
Potassium Chloride
Potassium Chloride Injection
40 mEq per 100 mL
400 mEq/L
100 mL STERILE SINGLE DOSE
CONTAINER EACH 100 mL CONTAINS
2.98 g POTASSIUM CHLORIDE pH 5 (4 TO
8) POTASSIUM 400 mEq/L CHLORIDE 400
mEq/L HYPERTONIC 799 mOsmol/L
(CALC) DOSAGE: SEE PRESCRIBING
INFORMATIONUSE ONLY WITH A
CALIBRATED INFUSION DEVICE USE
CENTRAL ROUTEWHENEVER POSSIBLE
DO NOT ADD SUPPLEMENTARY MEDICATION
STORE IN MOISTURE BARRIER OVERWRAP AT
ROOM TEMPERATURE (77°F or 25°C) UNTIL
READY TO USE Rx ONLY 0725004356

BAXTER Logo

USA 2B0824

Barcode FPO
(01)00303380703487

Container Label

Container Label

LOT EXP

NDC 0338-0709-48

Highly Concentrated (100 mEq/L)
Potassium Chloride
Potassium Chloride Injection
10 mEq per 100 mL
100 mEq/L
100 mL STERILE SINGLE DOSE
CONTAINER EACH 100 mL CONTAINS
746 mg POTASSIUM CHLORIDE pH 5 (4
TO 8) POTASSIUM 100 mEq/L CHLORIDE
100 mEq/L HYPERTONIC 200 mOsmol/L
(CALC) DOSAGE: SEE PRESCRIBING
INFORMATIONUSE ONLY WITH A
CALIBRATED INFUSION DEVICE USE
CENTRAL ROUTEWHENEVER POSSIBLE
DO NOT ADD SUPPLEMENTARY MEDICATION
STORE IN MOISTURE BARRIER OVERWRAP AT
ROOM TEMPERATURE (77°F or 25°C) UNTIL
READY TO USE Rx ONLY 0725004357

BAXTER Logo

USA 2B0826

Barcode FPO
(01)00303380709489

Container Label

Container Label

LOT EXP

NDC 0338-0705-48

Highly Concentrated (200 mEq/L)
Potassium Chloride
Potassium Chloride Injection
20 mEq per 100 mL
200 mEq/L
100 mL STERILE SINGLE DOSE
CONTAINER EACH 100 mL CONTAINS
1.49 g POTASSIUM CHLORIDE pH 5 (4 TO
8) POTASSIUM 200 mEq/L CHLORIDE 200
mEq/L HYPERTONIC 400 mOsmol/L
(CALC) DOSAGE: SEE PRESCRIBING
INFORMATION USE ONLY WITH A
CALIBRATED INFUSION DEVICE USE
CENTRAL ROUTE WHENEVER POSSIBLE DO
NOT ADD SUPPLEMENTARY MEDICATION
STORE IN MOISTURE BARRIER OVERWRAP AT
ROOM TEMPERATURE (77°F or 25°C) UNTIL
READY TO USE Rx ONLY 0725004358

BAXTER Logo

USA 2B0827

Barcode FPO
(01)00303380705481